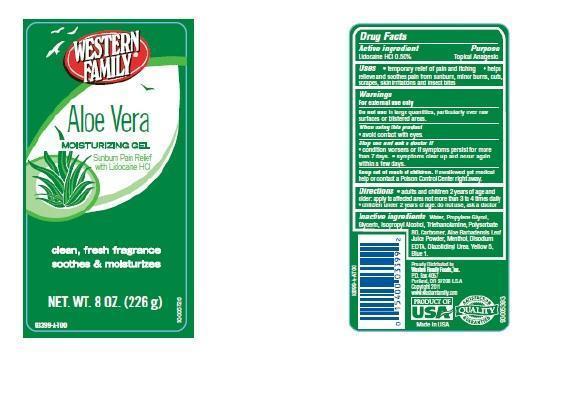 DRUG LABEL: Western Family Aloe Vera Moisturizing
NDC: 55312-012 | Form: GEL
Manufacturer: WESTERN FAMILY FOODS, INC.
Category: otc | Type: HUMAN OTC DRUG LABEL
Date: 20140702

ACTIVE INGREDIENTS: LIDOCAINE HYDROCHLORIDE 0.5 g/100 g
INACTIVE INGREDIENTS: WATER; PROPYLENE GLYCOL; GLYCERIN; ISOPROPYL ALCOHOL; TROLAMINE; POLYSORBATE 80; ALOE VERA LEAF; MENTHOL; EDETATE DISODIUM; DIAZOLIDINYL UREA; FD&C YELLOW NO. 5; FD&C BLUE NO. 1

Drug Facts

Active ingredient

Lidocaine HCl 0.5%

Purpose

Topical Analgesic

Uses

- temporary relief of pain and itching
- helps relieve and soothes pain from sunburn, minor burns, cuts, scrapes, skin irritations and insect bites

Warnings

For external use only

Do not use

in large quantities, particularly over raw surfaces or blistered areas.

When using this product

- avoid contact with eyes

Stop use and ask a doctor if

- condition worsens or if symptoms persist for more than 7 days.
- symptoms clear up and occur again within a few days.

Keep out of reach of children

If swallowed get medical help or contact a Poison Control Center right away

Directions

- adults and children 2 years of age and older: apply to affected areas not more than 3 to 4 times daily
- children under 2 years of age: do not use, ask a doctor

Inactive ingredients

Water, Propylene Glycol, Glycerin, Isopropyl Alcohol, Triethanolamine, Polysorbate 80, Carbomer, Aloe Barbadensis Leaf Juice Powder, Menthol, Disodium EDTA, Diazolidinyl Urea, Yellow 5, Blue 1.

Principal Display Panel

WESTERN FAMILY

Aloe Vera

MOISTURIZING GEL

Sunburn Pain Relief

with Lidocaine HCL

clean, fresh fragrance soothes and moisturizes

NET WT. 8 OZ. (226 g)